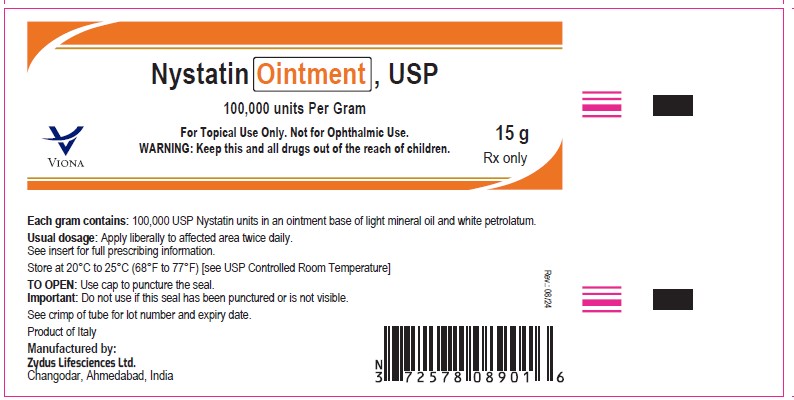 DRUG LABEL: Nystatin and Triamcinolone Acetonide
NDC: 70771-1447 | Form: OINTMENT
Manufacturer: Zydus Lifesciences Limited
Category: prescription | Type: HUMAN PRESCRIPTION DRUG LABEL
Date: 20240816

ACTIVE INGREDIENTS: NYSTATIN 100000 [USP'U]/1 g; TRIAMCINOLONE ACETONIDE 1 mg/1 g
INACTIVE INGREDIENTS: MINERAL OIL; PETROLATUM

Nystatin and Triamcinolone Acetonide Ointment, USP

PACKAGE LABEL.PRINCIPAL DISPLAY PANEL

NDC 70771-1447-1

Nystatin and Triamcinolone Acetonide Ointment, 15 gm

Rx only